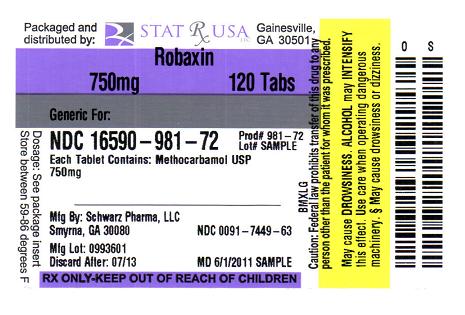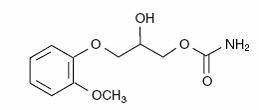 DRUG LABEL: ROBAXIN
NDC: 16590-981 | Form: TABLET, FILM COATED
Manufacturer: STAT RX USA LLC
Category: prescription | Type: HUMAN PRESCRIPTION DRUG LABEL
Date: 20110824

ACTIVE INGREDIENTS: METHOCARBAMOL 750 mg/1 1
INACTIVE INGREDIENTS: FD&C YELLOW NO. 6; HYDROXYPROPYL CELLULOSE; HYPROMELLOSES; MAGNESIUM STEARATE; POLYSORBATE 20; POVIDONE; PROPYLENE GLYCOL; SACCHARIN SODIUM; SODIUM LAURYL SULFATE; STEARIC ACID; TITANIUM DIOXIDE; D&C YELLOW NO. 10

Rx Only

DESCRIPTION

robaxin®/robaxin®-750 (methocarbamol tablets, USP), a carbamate derivative of guaifenesin, is a central nervous system (CNS) depressant with sedative and musculoskeletal relaxant properties.

The chemical name of methocarbamol is 3-(2-methoxyphenoxy)-1,2-propanediol 1-carbamate and has the empirical formula C11H15NO5. Its molecular weight is 241.24. The structural formula is shown below.

Methocarbamol is a white powder, sparingly soluble in water and chloroform, soluble in alcohol (only with heating) and propylene glycol, and insoluble in benzene and n-hexane.

robaxin® is available as a light orange, round, film-coated tablet containing 500 mg of methocarbamol, USP for oral administration. The inactive ingredients present are corn starch, FD and C Yellow 6, hydroxypropyl cellulose, hypromellose, magnesium stearate, polysorbate 20, povidone, propylene glycol, saccharin sodium, sodium lauryl sulfate, sodium starch glycolate, stearic acid, titanium dioxide.

robaxin®-750 is available as an orange capsule-shaped, film-coated tablet containing 750 mg of methocarbamol, USP for oral administration. In addition to the inactive ingredients present in robaxin®, robaxin®-750 also contains D and C Yellow 10.

CLINICAL PHARMACOLOGY

The mechanism of action of methocarbamol in humans has not been established, but may be due to general central nervous system (CNS) depression. It has no direct action on the contractile mechanism of striated muscle, the motor end plate or the nerve fiber.

Pharmacokinetics

In healthy volunteers, the plasma clearance of methocarbamol ranges between 0.20 and
0.80 L/h/kg, the mean plasma elimination half-life ranges between 1 and 2 hours, and the plasma protein binding ranges between 46% and 50%.

Methocarbamol is metabolized via dealkylation and hydroxylation. Conjugation of methocarbamol also is likely. Essentially all methocarbamol metabolites are eliminated in the urine. Small amounts of unchanged methocarbamol also are excreted in the urine.

Special populations
Elderly

The mean (± SD) elimination half-life of methocarbamol in elderly healthy volunteers (mean
(± SD) age, 69 (± 4) years) was slightly prolonged compared to a younger (mean (± SD) age,
53.3 (± 8.8) years), healthy population (1.5 (± 0.4) hours versus 1.1 (±0.27) hours, respectively). The fraction of bound methocarbamol was slightly decreased in the elderly versus younger volunteers (41 to 43% versus 46 to 50%, respectively).

Renally impaired

The clearance of methocarbamol in 8 renally-impaired patients on maintenance hemodialysis was reduced about 40% compared to 17 normal subjects, although the mean (± SD) elimination half-life in these two groups was similar: 1.2 (± 0.6) versus 1.1 (±0.3) hours, respectively.

Hepatically impaired

In 8 patients with cirrhosis secondary to alcohol abuse, the mean total clearance of methocarbamol was reduced approximately 70% compared to that obtained in 8 age- and
weight-matched normal subjects. The mean (± SD) elimination half-life in the cirrhotic patients and the normal subjects was 3.38 (± 1.62) hours and 1.11 (± 0.27) hours, respectively. The percent of methocarbamol bound to plasma proteins was decreased to approximately 40 to 45% compared to 46 to 50% in the normal subjects.

INDICATIONS AND USAGE

robaxin® and robaxin®-750 are indicated as an adjunct to rest, physical therapy, and other measures for the relief of discomfort associated with acute, painful musculoskeletal conditions. The mode of action of methocarbamol has not been clearly identified, but may be related to its sedative properties. Methocarbamol does not directly relax tense skeletal muscles in man.

CONTRAINDICATIONS

robaxin® and robaxin®-750 are contraindicated in patients hypersensitive to methocarbamol or to any of the tablet components.

WARNINGS

Since methocarbamol may possess a general CNS depressant effect, patients receiving robaxin® or robaxin®-750 should be cautioned about combined effects with alcohol and other CNS depressants.

Safe use of robaxin® and robaxin®-750 has not been established with regard to possible adverse effects upon fetal development. There have been reports of fetal and congenital abnormalities following in utero exposure to methocarbamol. Therefore, robaxin® and robaxin®-750 should not be used in women who are or may become pregnant and particularly during early pregnancy unless in the judgment of the physician the potential benefits outweigh the possible hazards (see PRECAUTIONS, Pregnancy).

Use In Activities Requiring Mental Alertness

Methocarbamol may impair mental and/or physical abilities required for performance of hazardous tasks, such as operating machinery or driving a motor vehicle. Patients should be cautioned about operating machinery, including automobiles, until they are reasonably certain that methocarbamol therapy does not adversely affect their ability to engage in such activities.

PRECAUTIONS

Information for Patients

Patients should be cautioned that methocarbamol may cause drowsiness or dizziness, which may impair their ability to operate motor vehicles or machinery.

Because methocarbamol may possess a general CNS-depressant effect, patients should be cautioned about combined effects with alcohol and other CNS depressants.

Drug Interactions

See WARNINGS and PRECAUTIONS for interaction with CNS drugs and alcohol.

Methocarbamol may inhibit the effect of pyridostigmine bromide. Therefore, methocarbamol should be used with caution in patients with myasthenia gravis receiving anticholinesterase agents.

Drug/Laboratory Test Interactions

Methocarbamol may cause a color interference in certain screening tests for
5-hydroxyindoleacetic acid (5-HIAA) using nitrosonaphthol reagent and in screening tests for urinary vanillylmandelic acid (VMA) using the Gitlow method.

Carcinogenesis, Mutagenesis, Impairment of Fertility

Long-term studies to evaluate the carcinogenic potential of methocarbamol have not been performed. No studies have been conducted to assess the effect of methocarbamol on mutagenesis or its potential to impair fertility.

Pregnancy
Teratogenic Effects
Pregnancy Category C

Animal reproduction studies have not been conducted with methocarbamol. It is also not known whether methocarbamol can cause fetal harm when administered to a pregnant woman or can affect reproduction capacity. robaxin® and robaxin®-750 should be given to a pregnant woman only if clearly needed.

Safe use of robaxin® and robaxin®-750 has not been established with regard to possible adverse effects upon fetal development. There have been reports of fetal and congenital abnormalities following in utero exposure to methocarbamol. Therefore, robaxin® and robaxin®-750 should not be used in women who are or may become pregnant and particularly during early pregnancy unless in the judgment of the physician the potential benefits outweigh the possible hazards (see WARNINGS).

Nursing Mothers

Methocarbamol and/or its metabolites are excreted in the milk of dogs; however, it is not known whether methocarbamol or its metabolites are excreted in human milk. Because many drugs are excreted in human milk, caution should be exercised when robaxin® or robaxin®-750 is administered to a nursing woman.

Pediatric Use

Safety and effectiveness of robaxin® and robaxin®-750 in pediatric patients below the age of 16 have not been established.

ADVERSE REACTIONS

Adverse reactions reported coincident with the administration of methocarbamol include:

Body as a whole: Anaphylactic reaction, angioneurotic edema, fever, headache

Cardiovascular system: Bradycardia, flushing, hypotension, syncope, thrombophlebitis

Digestive system: Dyspepsia, jaundice (including cholestatic jaundice), nausea and vomiting

Hemic and lymphatic system: Leukopenia

Immune system: Hypersensitivity reactions

Nervous system: Amnesia, confusion, diplopia, dizziness or lightheadedness, drowsiness, insomnia, mild muscular incoordination, nystagmus, sedation, seizures (including grand mal), vertigo

Skin and special senses: Blurred vision, conjunctivitis, nasal congestion, metallic taste, pruritus, rash, urticaria

OVERDOSAGE

Limited information is available on the acute toxicity of methocarbamol. Overdose of methocarbamol is frequently in conjunction with alcohol or other CNS depressants and includes the following symptoms: nausea, drowsiness, blurred vision, hypotension, seizures, and coma.

In post-marketing experience, deaths have been reported with an overdose of methocarbamol alone or in the presence of other CNS depressants, alcohol or psychotropic drugs.

Treatment

Management of overdose includes symptomatic and supportive treatment. Supportive measures include maintenance of an adequate airway, monitoring urinary output and vital signs, and administration of intravenous fluids if necessary. The usefulness of hemodialysis in managing overdose is unknown.

DOSAGE AND ADMINISTRATION

robaxin® (methocarbamol), 500 mg – Adults:
Initial dosage: 3 tablets q.i.d.
Maintenance dosage: 2 tablets q.i.d.
robaxin®-750 (methocarbamol): 750 mg – Adults:
Initial dosage: 2 tablets q.i.d.
Maintenance dosage: 1 tablet q.4h. or 2 tablets t.i.d.

Six grams a day are recommended for the first 48 to 72 hours of treatment. (For severe conditions 8 grams a day may be administered). Thereafter, the dosage can usually be reduced to approximately 4 grams a day.

HOW SUPPLIED

robaxin® (methocarbamol tablets, USP)
500 mg tablets are light orange, round, film-coated tablets engraved with ROBAXIN 500 on the unscored side and SP above the score on the other side. They are supplied as follows:

Bottles of 100 | NDC 0091-7429-63

robaxin®-750 (methocarbamol tablets, USP)
750 mg tablets are orange, capsule-shaped, film-coated tablets engraved with ROBAXIN 750 on one side and SP on the other. They are supplied as follows:

Bottles of 100 | NDC 0091-7449-63
Bottles of 500 | NDC 0091-7449-70

Store at controlled room temperature, between 20°C and 25°C (68°F and 77°F).
Dispense in tight container.

Manufactured for:
SCHWARZ PHARMA, LLC
a subsidiary of UCB, Inc.
Smyrna, GA 30080

Printed in USA

Rev. 1E 09/2009